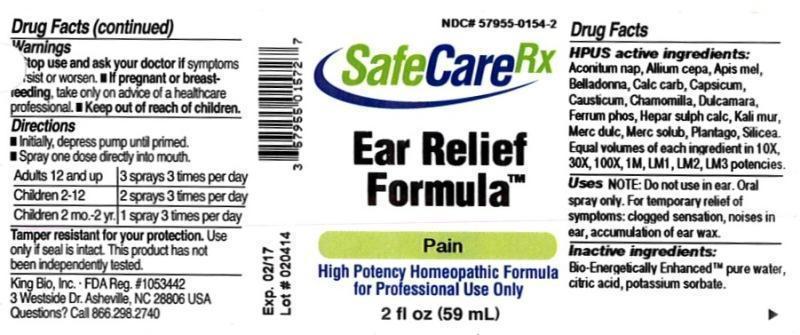 DRUG LABEL: Ear Relief Formula
NDC: 57955-0154 | Form: LIQUID
Manufacturer: King Bio Inc.
Category: homeopathic | Type: HUMAN OTC DRUG LABEL
Date: 20150304

ACTIVE INGREDIENTS: ACONITUM NAPELLUS 10 [hp_X]/59 mL; ONION 10 [hp_X]/59 mL; APIS MELLIFERA 10 [hp_X]/59 mL; ATROPA BELLADONNA 10 [hp_X]/59 mL; OYSTER SHELL CALCIUM CARBONATE, CRUDE 10 [hp_X]/59 mL; CAPSICUM 10 [hp_X]/59 mL; CAUSTICUM 10 [hp_X]/59 mL; MATRICARIA RECUTITA 10 [hp_X]/59 mL; SOLANUM DULCAMARA TOP 10 [hp_X]/59 mL; FERROSOFERRIC PHOSPHATE 10 [hp_X]/59 mL; CALCIUM SULFIDE 10 [hp_X]/59 mL; POTASSIUM CHLORIDE 10 [hp_X]/59 mL; CALOMEL 10 [hp_X]/59 mL; MERCURIUS SOLUBILIS 10 [hp_X]/59 mL; PLANTAGO MAJOR 10 [hp_X]/59 mL; SILICON DIOXIDE 10 [hp_X]/59 mL
INACTIVE INGREDIENTS: WATER; ANHYDROUS CITRIC ACID; POTASSIUM SORBATE

Ear Relief Formula™

ACTIVE INGREDIENT

Drug Facts__________________________________________________________________________________________________________

HPUS active ingredients: Aconitum napellus, Allium cepa, Apis mellifica, Belladonna, Calcarea carbonica, Capsicum annuum, Causticum, Chamomilla, Dulcamara, Ferrum phosphoricum, Hepar sulphuris calcareum, Kali muriaticum, Mercurius dulcis, Mercurius solubilis, Plantago major, Silicea. Equal volumes of each ingredient in 10X, 30X, 100X, 1M, LM1, LM2, LM3 potencies.

INDICATIONS AND USAGE

Uses NOTE: Do not use in ear. Oral spray only. For temporary relief of symptoms: clogged sensation, noises in ear, accumulation of ear wax.

Inactive Ingredients:

Bio-Energetically Enhanced™ pure water, citric acid and potassium sorbate.

Warnings

- Stop use and ask your doctor if symptoms persist or worsen.
- If pregnant or breast-feeding, take only on advice of a healthcare professional.

- Keep out of reach of children.

Directions

- Initially, depress pump until primed.
- Spray one dose directly into mouth.
- Adults 12 and up: 3 sprays 3 times per day
- Children 2-12: 2 sprays 3 times per day
- Children 2 mo.-2 yr.: 1 spray 3 times per day

OTHER SAFETY INFORMATION

Tamper resistant for your protection. Use only if safety seal is intact. This product has not been independently tested.

PURPOSE

Uses NOTE: Do not use in ear. Oral spray only. For temporary relief of symptoms:

- clogged sensation
- noises in ear
- accumulation of ear wax